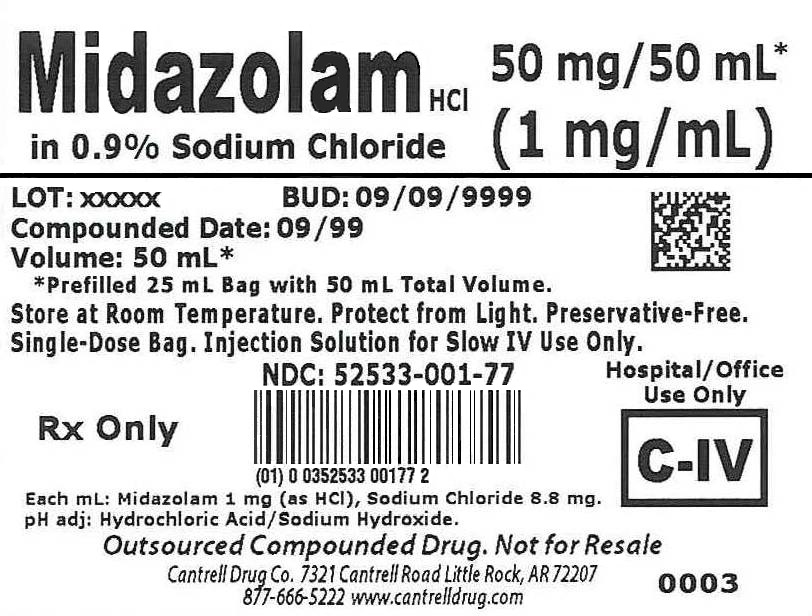 DRUG LABEL: Midazolam HCl
NDC: 52533-001 | Form: INJECTION, SOLUTION
Manufacturer: Cantrell Drug Company
Category: prescription | Type: HUMAN PRESCRIPTION DRUG LABEL
Date: 20160406
DEA Schedule: CIV

ACTIVE INGREDIENTS: MIDAZOLAM HYDROCHLORIDE 1 mg/1 mL
INACTIVE INGREDIENTS: SODIUM CHLORIDE 8.8 mg/1 mL; WATER

Midazolam HCl 1 mg/mL in 0.9% Sodium Chloride 50 mL Bag